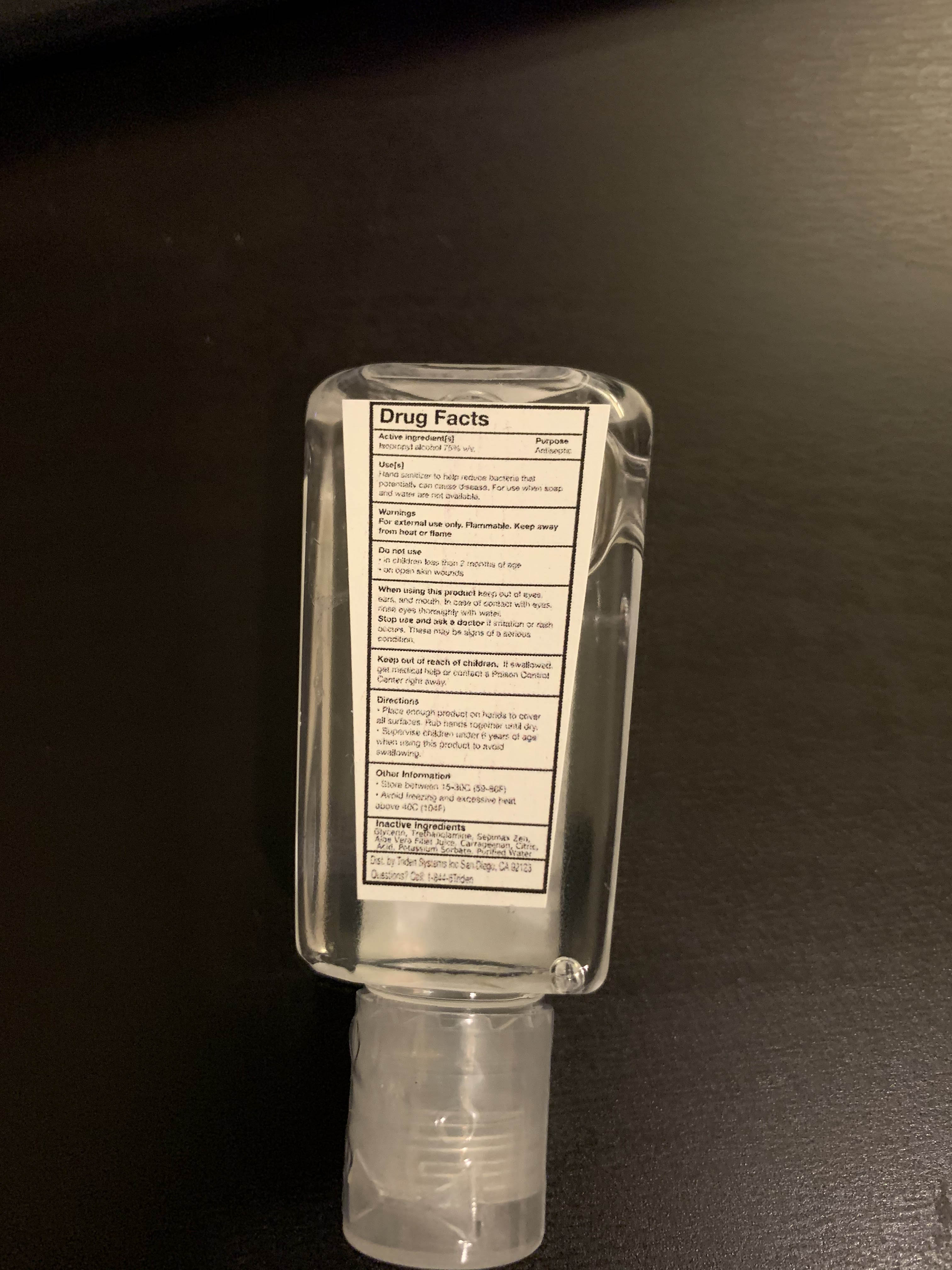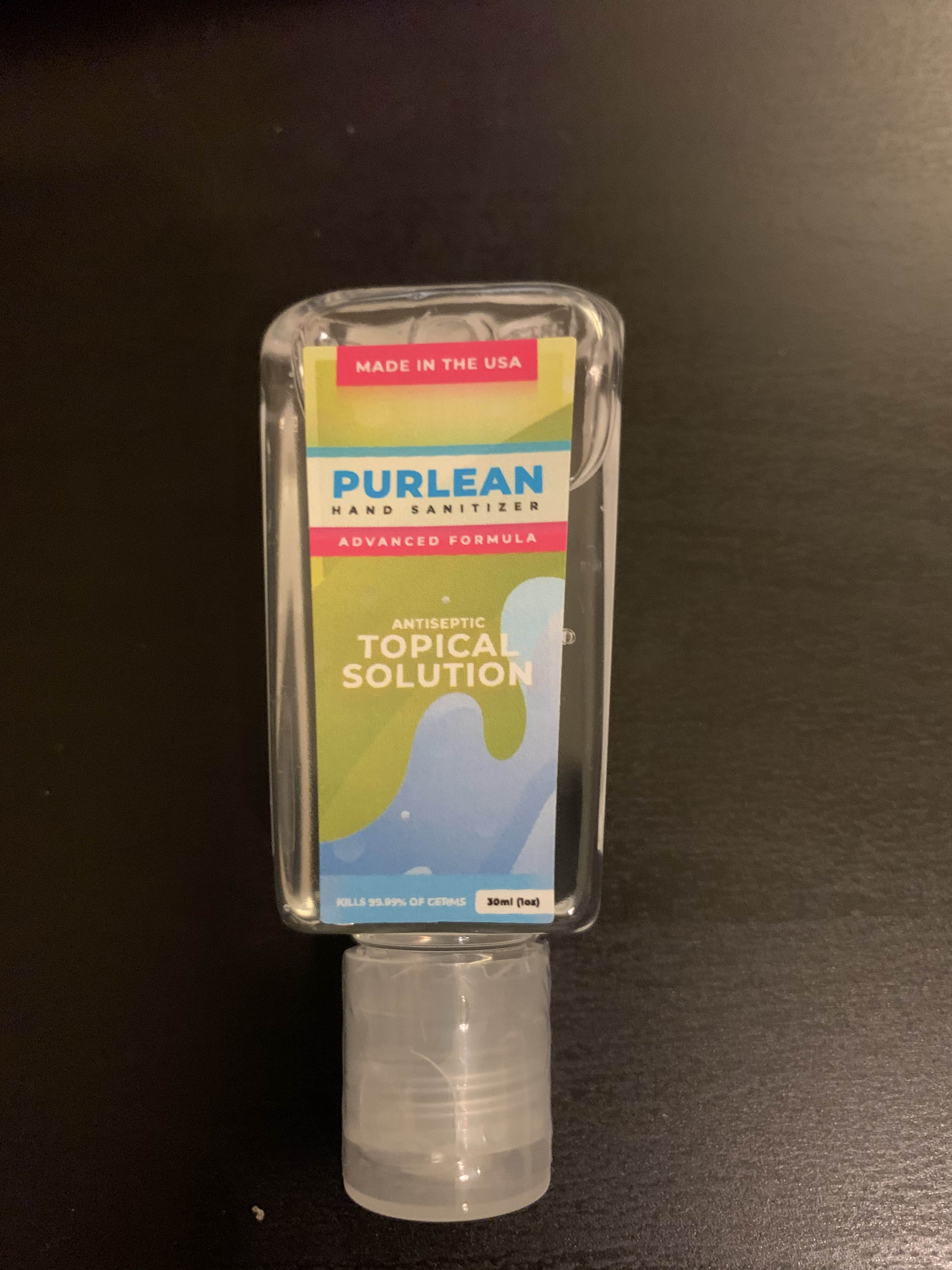 DRUG LABEL: Purlean Hand Sanitizer
NDC: 79046-001 | Form: GEL
Manufacturer: Triden Systems, Inc.
Category: otc | Type: HUMAN OTC DRUG LABEL
Date: 20200620

ACTIVE INGREDIENTS: ISOPROPYL ALCOHOL 70 g/100 g
INACTIVE INGREDIENTS: Propanediol 5 g/100 g; AMMONIUM ACRYLOYLDIMETHYLTAURATE, DIMETHYLACRYLAMIDE, LAURYL METHACRYLATE AND LAURETH-4 METHACRYLATE COPOLYMER, TRIMETHYLOLPROPANE TRIACRYLATE CROSSLINKED (45000 MPA.S) 1.2 g/100 g; WATER

This is a hand sanitizer manufactured according to the institute of personal care science.

The hand sanitizer is manufactured using only the following United States Pharmacopoeia (USP) grade ingredients.

1. Isopropyl Alcohol (70% w/w) in an aqueous solution denatured according to Alcohol and Tobacco Tax and Trade Bureau regulations in 27 CFR part 20.
2. 1,3 Propanediol (5.0% w/w).
3. Sepimax Zen (1.2% w/w).
4. Sterile distilled water

The firm does not add other active or inactive ingredients.

Active Ingredient(s)

Isopropyl Alcohol 70% w/w. Purpose: Antiseptic

Purpose

Antiseptic, Hand Sanitizer

Use

Hand Sanitizer to help reduce bacteria that potentially can cause disease. For use when soap and water are not available.

Warnings

For external use only. Flammable. Keep away from heat or flame

Do not use

- in children less than 2 months of age
- on open skin wounds

When using this product keep out of eyes, ears, and mouth. In case of contact with eyes, rinse eyes thoroughly with water.
Stop use and ask a doctor if irritation or rash occurs. These may be signs of a serious condition.
Keep out of reach of children. If swallowed, get medical help or contact a Poison Control Center right away.

Stop use and ask a doctor if irritation or rash occurs. These may be signs of a serious condition.

Keep out of reach of children. If swallowed, get medical help or contact a Poison Control Center right away.

Directions

- Place enough product on hands to cover all surfaces. Rub hands together until dry.
- Supervise children under 6 years of age when using this product to avoid swallowing.

Other information

- Store between 15-30C (59-86F)
- Avoid freezing and excessive heat above 40C (104F)

Inactive ingredients

1,3 Propanediol, Sepimax Zen, purified water USP

Package Label - Principal Display Panel

30 ml NDC: 79046-001-01